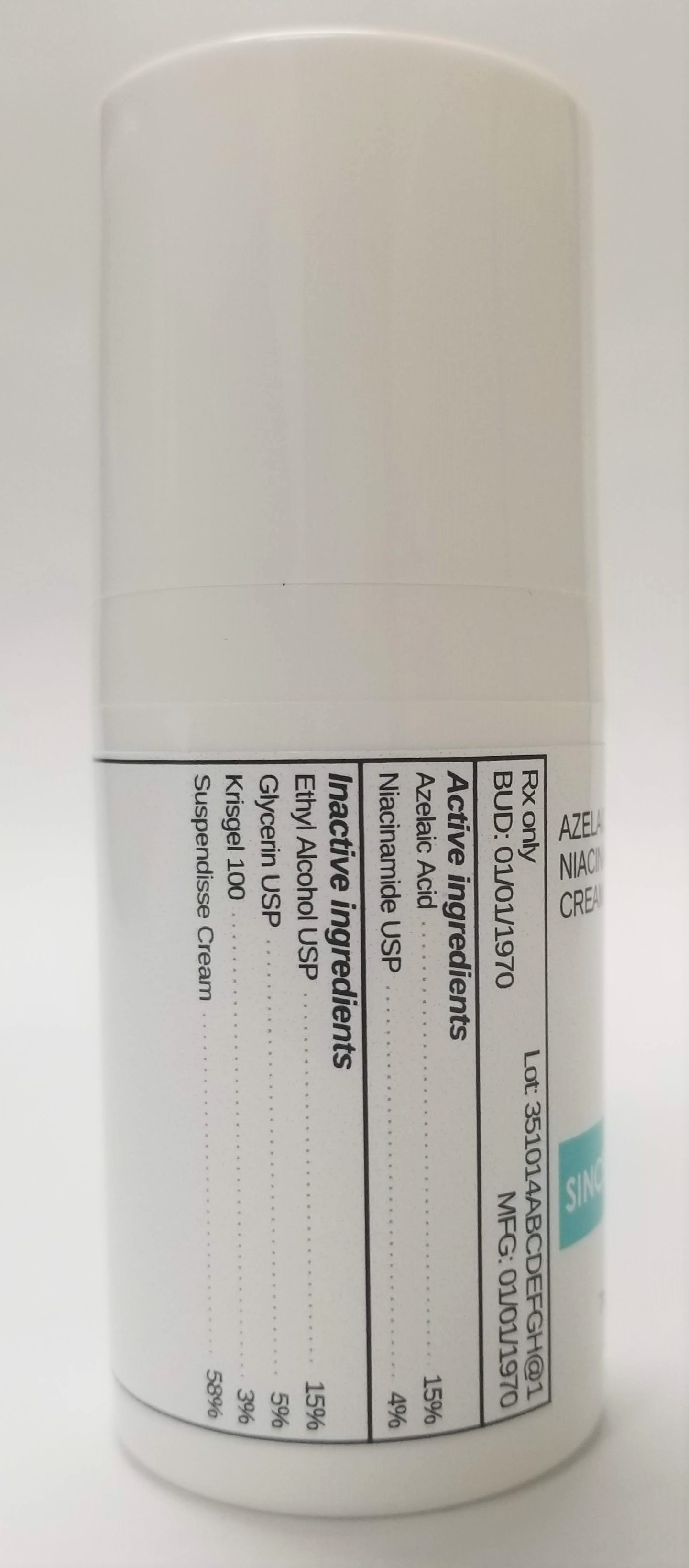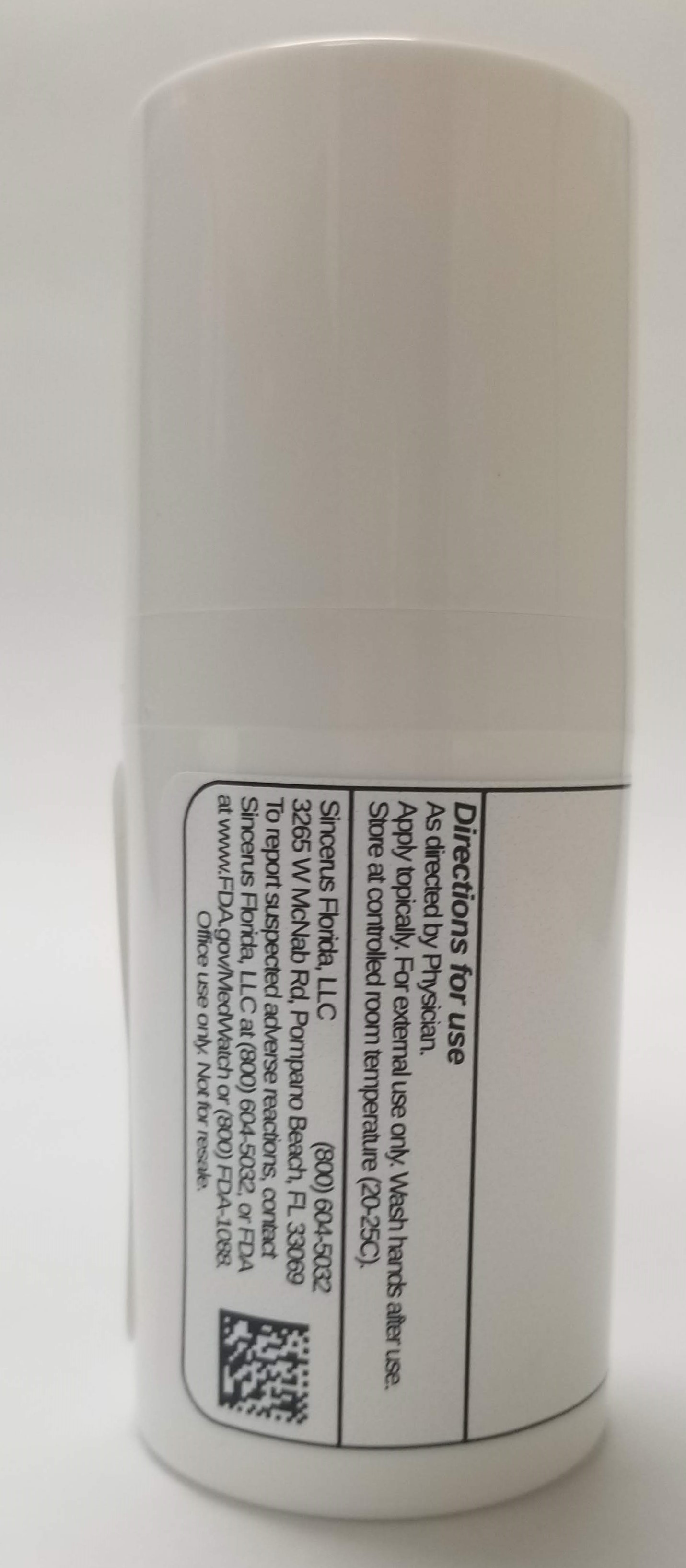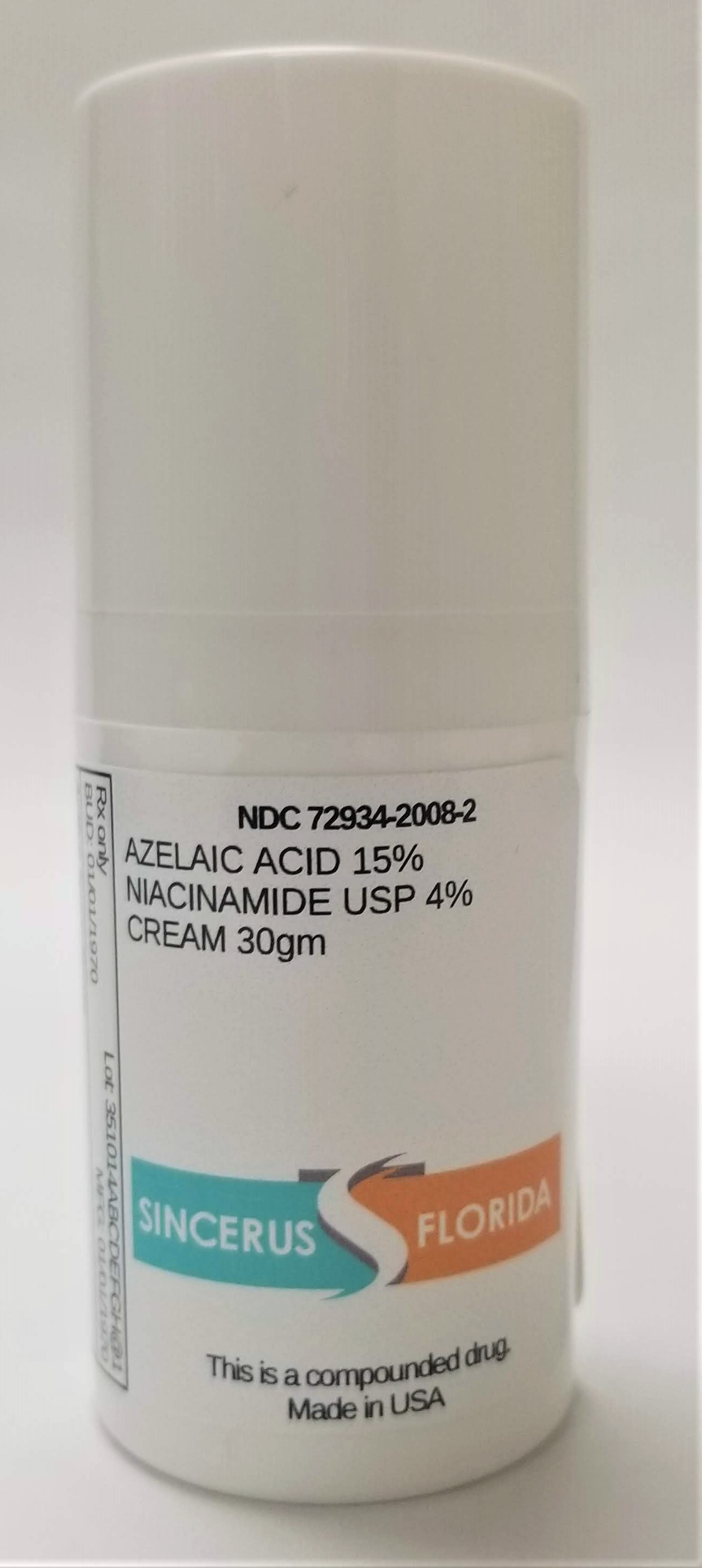 DRUG LABEL: AZELAIC ACID 15% / NIACINAMIDE 4%
NDC: 72934-2008 | Form: CREAM
Manufacturer: Sincerus Florida, LLC
Category: prescription | Type: HUMAN PRESCRIPTION DRUG LABEL
Date: 20190423

ACTIVE INGREDIENTS: AZELAIC ACID 15 g/100 g; NIACINAMIDE 4 g/100 g

AZELAIC ACID 15% / NIACINAMIDE 4%